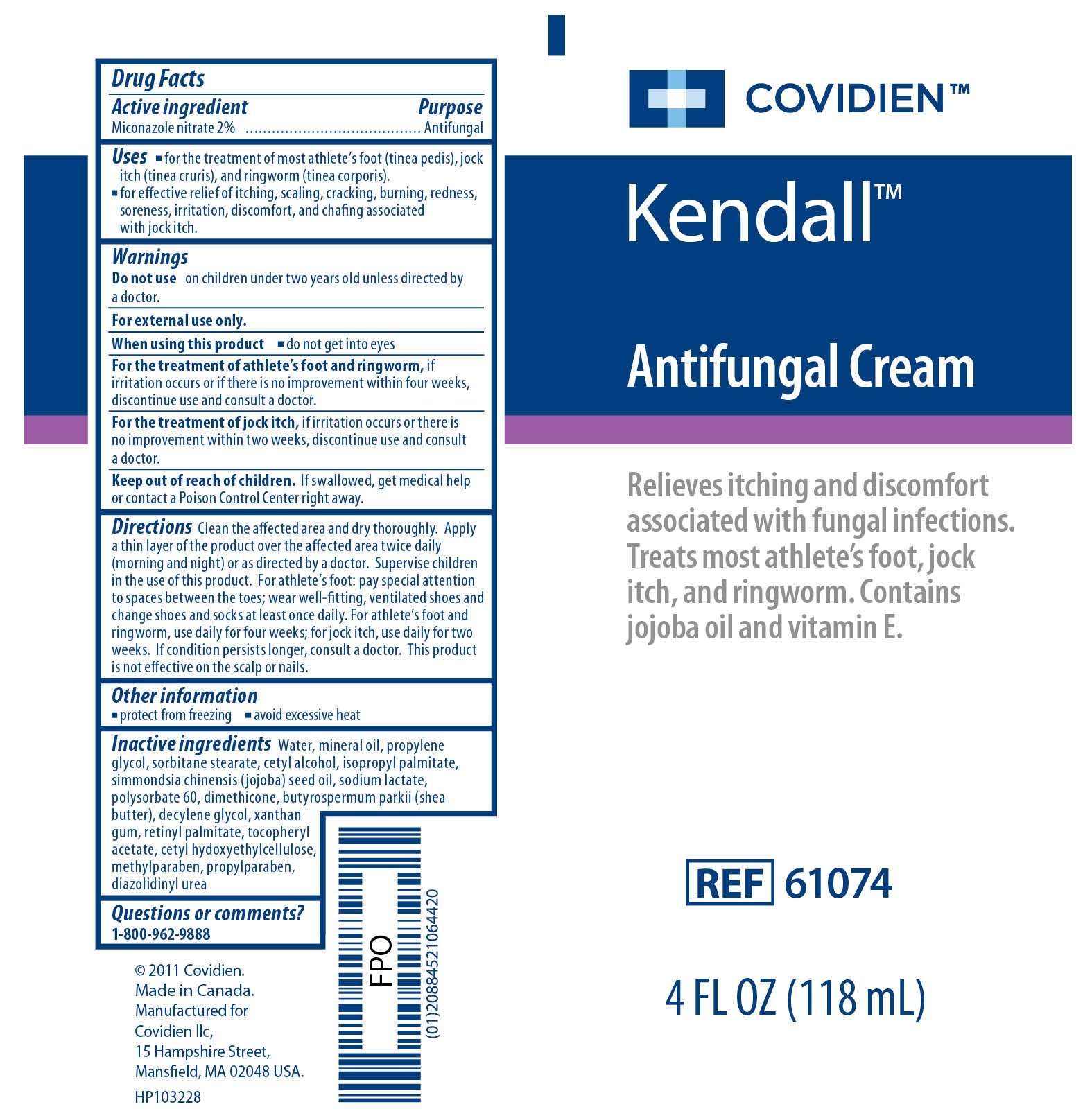 DRUG LABEL: Kendall Antifungal 
NDC: 28851-692 | Form: CREAM
Manufacturer: Covidien Inc.
Category: otc | Type: HUMAN OTC DRUG LABEL
Date: 20110414

ACTIVE INGREDIENTS: MICONAZOLE NITRATE 2 g/100 g
INACTIVE INGREDIENTS: Water; MINERAL OIL; PROPYLENE GLYCOL ; SORBITAN MONOSTEARATE; CETYL ALCOHOL; ISOPROPYL PALMITATE; SODIUM LACTATE; JOJOBA OIL; POLYSORBATE 60; VITAMIN A PALMITATE; DIMETHICONE; SHEA BUTTER; CETYL HYDROXYETHYLCELLULOSE (350000 MW); METHYLPARABEN; 1-DECENE; PROPYLPARABEN ; DIAZOLIDINYL UREA; XANTHAN GUM; ALPHA-TOCOPHEROL ACETATE

Kendall Antifungal Cream

Active Ingredient

Miconazole nitrate 2%

Purpose

Antifungal

Uses

- for the treatment of most athlete's foot (tinea pedis), jock itch (tinea cruris), and ringworm (tinea corporis).
- for effective relief of itching, scaling, cracking, burning, redness, soreness, irritation, discomfort, and chafing associated with jock itch.

Warnings

Do not use on children under two years old unless directed by a doctor.

For external use only.
When using this product

- do not get into eyes

For the treatment of athlete's foot and ringworm, if irritation occurs or if there is no improvement within four weeks, discontinue use and consult a doctor.
For the treatment of jock itch, if irritation occurs or if there is no improvement within two weeks, discontinue use and consult a doctor.
Keep out of the reach of children. If swallowed, get medical help or contact a Poison Control Center right away.

DOSAGE AND ADMINISTRATION

Directions Clean the affected area and dry thoroughly. Apply a thin layer of the product over the affected area twice daily (morning and night) or as directed by a doctor. Supervise children in the use of this product. For athlete's foot: pay special attention to spaces between the toes; wear well-fitting, ventilated shoes and change shoes and socks at least once daily. For athlete's foot and ringworm, use daily for four weeks; for jock itch, use daily for two weeks. If condition persists longer, consult a doctor. This product is not effective on the scalp or nails.

Other Information

- protect from freezing
- avoid excessive heat

Inactive ingredients

Water, mineral oil propylene glycol, sorbitane stearate, cetyl alcohol, isopropyl palmitate, simmondsia chinensis (jojoba) seed oil, sodium lactate, polysorbate 60, dimethicone, butyrospermum parkii (shea butter), decylene glycol, xanthan gum, retinyl palmitate, tocopheryl acetate, cetyl hydroxyethylcellulose, methylparaben, propylparaben, diazolidinyl urea

Questions or comments? 1-800-962-9888

Image of Antifungal Cream 4 oz Label